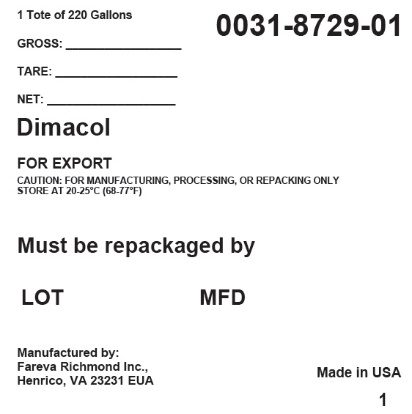 DRUG LABEL: Dimacol
NDC: 0031-8729 | Form: SYRUP
Manufacturer: Haleon US Holdings LLC
Category: other | Type: BULK INGREDIENT
Date: 20240423

ACTIVE INGREDIENTS: DEXTROMETHORPHAN HYDROBROMIDE 10 mg/5 mL; GUAIFENESIN 100 mg/5 mL; PHENYLEPHRINE HYDROCHLORIDE 5 mg/5 mL
INACTIVE INGREDIENTS: SODIUM BENZOATE; GLYCERIN; SORBITOL; PROPYLENE GLYCOL; ANHYDROUS CITRIC ACID; MENTHOL, UNSPECIFIED FORM; SUCRALOSE; FD&C RED NO. 40; WATER

Dimacol

PRINCIPAL DISPLAY PANEL - Shipping Label

1 Tote of 220 Gallons

0031-8729-01

GROSS: __________________

TARE: ___________________

NET: ____________________

Dimacol

FOR EXPORT

CAUTION: FOR MANUFACTURING, PROCESSING, OR REPACKING ONLY
STORE AT 20-25°C (68-77°F)

Must be repackaged by

LOT
MFD

Manufactured by:
Fareva Richmond Inc.,
Henrico, VA 23231 EUA

Made in USA

1